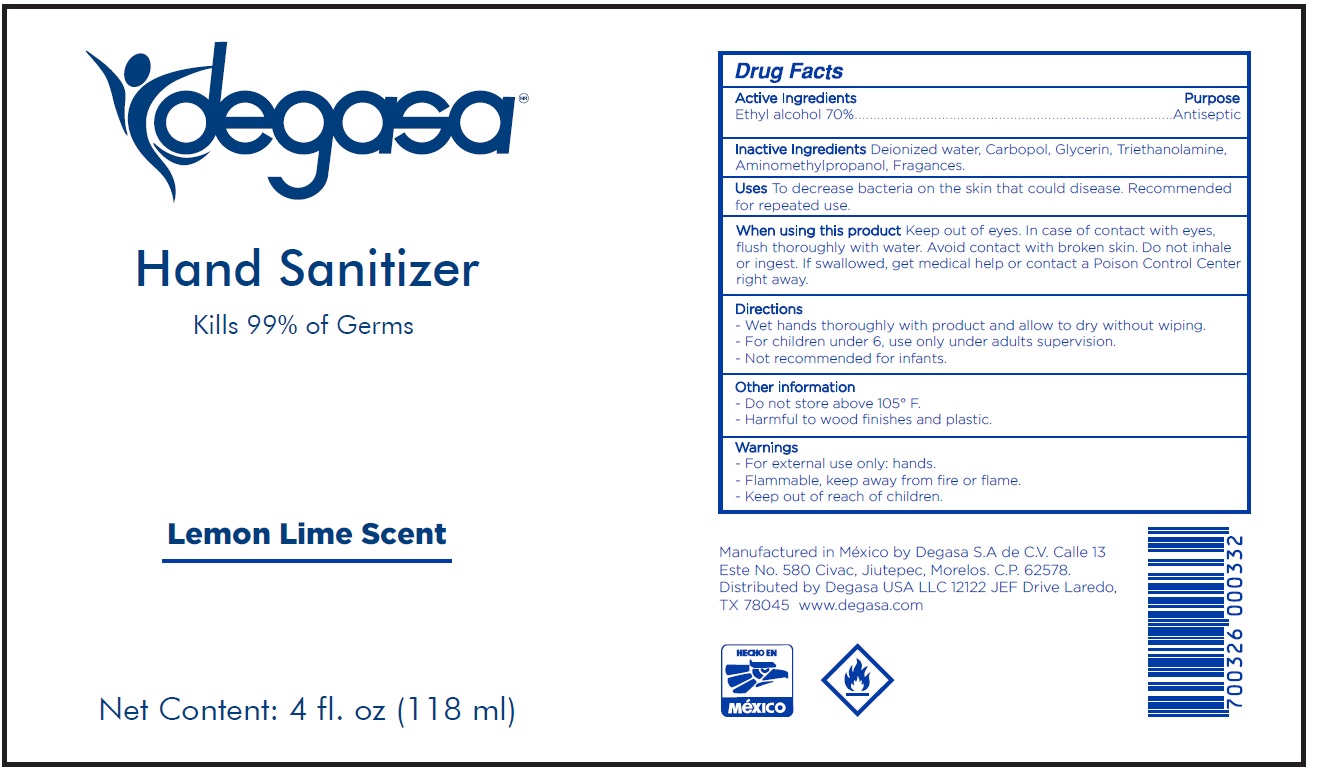 DRUG LABEL: Hand Sanitizer
NDC: 67326-005 | Form: GEL
Manufacturer: Degasa, S.A. de C.V.
Category: otc | Type: HUMAN OTC DRUG LABEL
Date: 20231109

ACTIVE INGREDIENTS: ALCOHOL 0.7 mL/1 mL
INACTIVE INGREDIENTS: WATER; CARBOMER HOMOPOLYMER, UNSPECIFIED TYPE; GLYCERIN; TROLAMINE; AMINOMETHYLPROPANOL

Hand Sanitizer

Active ingredients

Ethyl alcohol 70%

Purpose

Antiseptic

Inactive Ingredients

Deionized water, Carbopol, Glycerin, Triethanolamine, Aminomethylpropanol, Fragances.

Uses

To decrease bacteria on the skin that could disease. Recommended for repeated use.

When using this product

Keep out of eyes. In case of contact with eyes, flush thoroughly with water. Avoid contact with broken skin.
Do not inhale or ingest.

KEEP OUT OF REACH OF CHILDREN

If swallowed, get medical help or contact a Poison Control Center right away.

Directions

- Wet hands thoroughly with product and allow to dry without wiping.
- For children under 6, use only under adults supervision.
- Not recommended for infants

Other information

- Do not store above 105° F.
- Harmful to wood finishes and plastic.

Warnings

- For external use only: hands.
- Flammable, keep away from fire or flame.
- Keep out of reach of children.